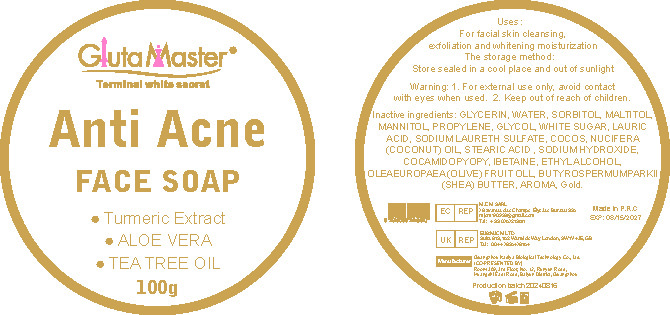 DRUG LABEL: Anti AcneSOAP
NDC: 84423-034 | Form: SOAP
Manufacturer: Guangzhou Kadiya Biotechnology Co., Ltd.
Category: otc | Type: HUMAN OTC DRUG LABEL
Date: 20240825

ACTIVE INGREDIENTS: GOLD 0.1 g/100 g; OLEA EUROPAEA (OLIVE) OIL UNSAPONIFIABLES 0.5 g/100 g
INACTIVE INGREDIENTS: LAURIC ACID; GLYCERIN; SODIUM LAURETH SULFATE; PROPYLENE GLYCOL; STEARIC ACID; WATER; COCO/OLEAMIDOPROPYL BETAINE; SHEA BUTTER; ALCOHOL; SORBITOL; MALTITOL; SODIUM HYDROXIDE; SUCROSE; COCONUT OIL

PURPOSE

For cleansing, exfoliating, brightening and moisturising the skin.

INACTIVE INGREDIENT

GLYCERIN、WATER、SORBITOL、MALTITOL、MANNITOL、PROPYLENE、GLYCOL、WHITE SUGAR、LAURIC ACID、SODIUM LAURETH SULFATE、COCOS、NUCIFERA(COCONUT)OIL、STEARIC ACID 、SODIUM HYDROXIDE、COCAMIDOPYOPY、IBETAINE、ETHYL ALCOHOL、BUTYROSPERMUMPARKII(SHEA)BUTTER、AROMA、

WARNINGS

1.Before use, perform a skin test on your arm and discontinue use if you have allergy symptoms or skin abnormalities.
2、For external use only, avoid contact with eyes when used
3、Keep out of reach of children

INDICATIONS AND USAGE

For facial skin cleansing,
exfoliation and whitening moisturization

DOSAGE AND ADMINISTRATION

For facial skin cleansing,
exfoliation and whitening moisturization

KEEP OUT OF REACH OF CHILDREN SECTION

Active Ingredients
OLEAEUROPAEA(OLIVE)FRUIT OLL0.5%
Gold 0.1%

PACKAGE LABEL

Active Ingredients
OLEAEUROPAEA(OLIVE)FRUIT OLL0.5%
Gold 0.1%

Uses：
For cleansing, exfoliating, brightening and moisturising the skin.
The storage method：
Store sealed in a cool place and out of sunlight

Warning.
1.Before use, perform a skin test on your arm and discontinue use if you have allergy symptoms or skin abnormalities.
2、For external use only, avoid contact with eyes when used
3、Keep out of reach of children

Inactive ingredients：
GLYCERIN、WATER、SORBITOL、MALTITOL、MANNITOL、PROPYLENE、GLYCOL、WHITE SUGAR、LAURIC ACID、SODIUM LAURETH SULFATE、COCOS、NUCIFERA(COCONUT)OIL、STEARIC ACID 、SODIUM HYDROXIDE、COCAMIDOPYOPY、IBETAINE、ETHYL ALCOHOL、BUTYROSPERMUMPARKII(SHEA)BUTTER、AROMA、